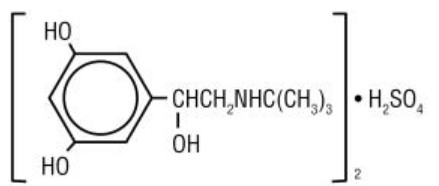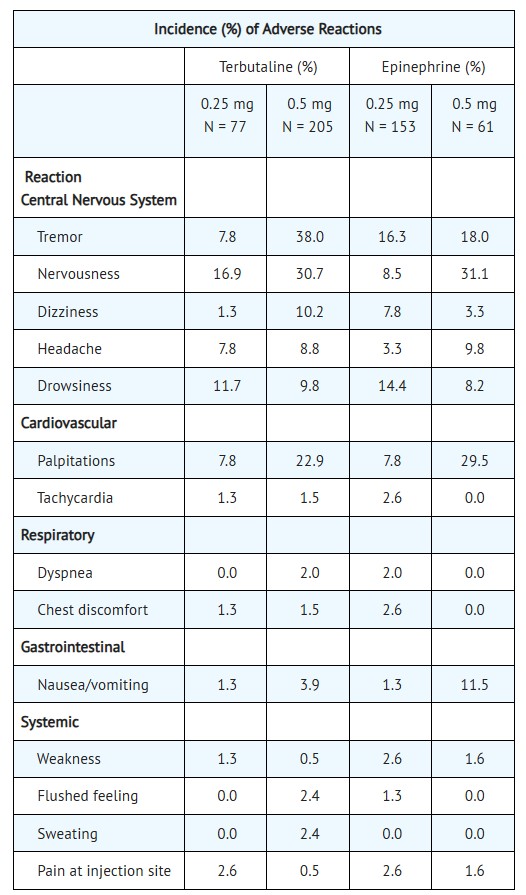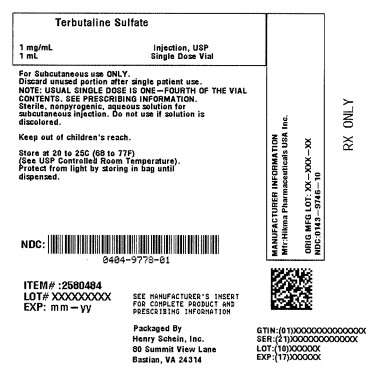 DRUG LABEL: Terbutaline Sulfate
NDC: 0404-9778 | Form: INJECTION
Manufacturer: Henry Schein, Inc.
Category: prescription | Type: HUMAN PRESCRIPTION DRUG LABEL
Date: 20250828

ACTIVE INGREDIENTS: TERBUTALINE SULFATE 1 mg/1 mL
INACTIVE INGREDIENTS: EDETATE DISODIUM; HYDROCHLORIC ACID; SODIUM CHLORIDE

TERBUTALINE SULFATE INJECTION

A sterile aqueous solution for subcutaneous injection

Rx Only

Boxed Warning

WARNING: PROLONGED TOCOLYSIS
Terbutaline sulfate has not been approved and should not be used for prolonged tocolysis (beyond 48-72 hours). In particular, terbutaline sulfate should not be used for maintenance tocolysis in the outpatient or home setting. Serious adverse reactions, including death, have been reported after administration of terbutaline sulfate to pregnant women. In the mother, these adverse reactions include increased heart rate, transient hyperglycemia, hypokalemia, cardiac arrhythmias, pulmonary edema and myocardial ischemia. Increased fetal heart rate and neonatal hypoglycemia may occur as a result of maternal administration (see CONTRAINDICATIONS: Prolonged Tocolysis).

Description

Terbutaline Sulfate, USP, the active ingredient of Terbutaline Sulfate Injection, USP, is a beta‑adrenergic agonist bronchodilator available as a sterile, nonpyrogenic, aqueous solution in vials, for subcutaneous administration. Each milliliter of solution contains 1 mg of Terbutaline Sulfate, USP (0.82 mg of the free base), sodium chloride for isotonicity, 0.055% edetate disodium dihydrate as a stabilizing agent, and hydrochloric acid for adjustment to a target pH of 4. Terbutaline sulfate is (±)-α-[(tert‑butylamino) methyl]-3,5-dihydroxybenzyI alcohol sulfate (2:1) (salt). The molecular formula is (C12H19N03)2•H2SO4 and the structural formula is:

Terbutaline Sulfate, USP is a white to gray-white crystalline powder. It is odorless or has a faint odor of acetic acid. It is soluble in water and in 0.1N hydrochloric acid, slightly soluble in methanol, and insoluble in chloroform. Its molecular weight is 548.65.

Clinical Pharmacology

Terbutaline sulfate injection is a beta-adrenergic receptor agonist. In vitro and in vivo pharmacologic studies have demonstrated that terbutaline exerts a preferential effect on beta2‑adrenergic receptors. While it is recognized that beta2-adrenergic receptors are the predominant receptors in bronchial smooth muscle, data indicate that there is a population of beta2-receptors in the human heart, existing in a concentration between 10% to 50%. The precise function of these receptors has not been established (see WARNINGS). Controlled clinical studies in patients given terbutaline subcutaneously have not revealed a preferential beta2-adrenergic effect.

The pharmacologic effects of beta-adrenergic agonists, including terbutaline, are at least in part attributable to stimulation through beta-adrenergic receptors of intracellular adenyl cyclase, the enzyme which catalyzes the conversion of adenosine triphosphate (ATP) to cyclic 3’,5’-adenosine monophosphate (cAMP). Increased cAMP levels are associated with relaxation of bronchial smooth muscle and inhibition of release of mediators of immediate hypersensitivity from cells, especially from mast cells.

Controlled clinical studies have shown that terbutaline sulfate injection relieves bronchospasm in acute and chronic obstructive pulmonary disease by significantly increasing pulmonary flow rates (e.g., an increase of 15% or more in FEV1). After subcutaneous administration of 0.25 mg of terbutaline sulfate injection, a measurable change in expiratory flow rate usually occurs within 5 minutes, and a clinically significant increase in FEV1 occurs within 15 minutes. The maximum effect usually occurs within 30 to 60 minutes, and clinically significant bronchodilator activity may continue for 1.5 to 4 hours. The duration of clinically significant improvement is comparable to that observed with equimilligram doses of epinephrine.

Preclinical
Studies in laboratory animals (minipigs, rodents, and dogs) have demonstrated the occurrence of cardiac arrhythmias and sudden death (with histological evidence of myocardial necrosis) when beta-agonists and methylxanthines are administered concurrently. The clinical significance of these findings is unknown.

Pharmacokinetics
Subcutaneous administration of 0.5 mg of terbutaline sulfate to 17 healthy, adult, male subjects resulted in mean (SD) peak plasma terbutaline concentration of 9.6 (3.6) ng/mL, which was observed at a median (range) time of 0.5 (0.08 to 1.0) hours after dosing. The mean (SD) AUC (0 to 48) and total body clearance values were 29.4 (14.2) hr•ng/mL, and 311 (112) mL/min respectively. The terminal half-life was determined in 9 of the 17 subjects and had a mean (SD) of 5.7 (2.0) hours.

After subcutaneous administration of 0.25 mg of terbutaline sulfate to two male subjects, peak terbutaline serum concentrations of 5.2 and 5.3 ng/mL were observed at about 20 minutes after dosing.

Elimination half-life of the drug in 10 of 14 patients was approximately 2.9 hours after subcutaneous administration, but longer elimination half-lives (between 6 to 14 hours) were found in the other 4 patients. About 90% of the drug was excreted in the urine at 96 hours after subcutaneous administration, with about 60% of this being unchanged drug. It appears that the sulfate conjugate is a major metabolite of terbutaline and urinary excretion is the primary route of elimination.

Indications and Usage

Terbutaline Sulfate Injection, USP is indicated for the prevention and reversal of bronchospasm in patients 12 years of age and older with asthma and reversible bronchospasm associated with bronchitis and emphysema.

Contraindications

1. Prolonged Tocolysis
Terbutaline sulfate has not been approved and should not be used for prolonged tocolysis (beyond 48-72 hours). In particular, terbutaline sulfate should not be used for maintenance tocolysis in the outpatient or home setting (see BOXED WARNING: Prolonged Tocolysis).

2. Hypersensitivity
Terbutaline sulfate injection is contraindicated in patients known to be hypersensitive to sympathomimetic amines or any component of this drug product.

Warnings

Deterioration of Asthma
Asthma may deteriorate acutely over a period of hours or chronically over several days or longer. If the patient needs more doses of terbutaline sulfate than usual, this may be a marker of destabilization of asthma and requires reevaluation of the patient and treatment regimen, giving special consideration to the possible need for anti‑inflammatory treatment, e.g., corticosteroids.

Use of Anti-Inflammatory Agents
The use of beta-adrenergic agonist bronchodilators alone may not be adequate to control asthma in many patients. Early consideration should be given to adding anti‑inflammatory agents, e.g., corticosteroids.

Cardiovascular Effects
Terbutaline sulfate, like all other beta-adrenergic agonists, can produce a clinically significant cardiovascular effect in some patients as measured by pulse rate, blood pressure, and/or symptoms. Although such effects are uncommon after administration of terbutaline sulfate at recommended doses, if they occur, the drug may need to be discontinued. In addition, beta‑agonists have been reported to produce electrocardiogram (ECG) changes, such as flattening of the T wave, prolongation of the QTc interval, and ST segment depression. The clinical significance of these findings is unknown. Therefore, terbutaline sulfate, like all sympathomimetic amines, should be used with caution in patients with cardiovascular disorders, especially coronary insufficiency, cardiac arrhythmias, and hypertension.

Seizures
There have been rare reports of seizures in patients receiving terbutaline; seizures did not recur in these patients after the drug was discontinued.

Precautions

General
Terbutaline, as with all sympathomimetic amines, should be used with caution in patients with cardiovascular disorders, including ischemic heart disease, hypertension, and cardiac arrhythmias; in patients with hyperthyroidism or diabetes mellitus; and in patients who are unusually responsive to sympathomimetic amines or who have convulsive disorders. Significant changes in systolic and diastolic blood pressure have been seen and could be expected to occur in some patients after use of any beta-adrenergic bronchodilator.

Immediate hypersensitivity reactions and exacerbations of bronchospasm have been reported after terbutaline administration.

Beta-adrenergic agonist medications may produce significant hypokalemia in some patients, possibly through intracellular shunting, which has the potential to produce adverse cardiovascular effects. The decrease is usually transient, not requiring supplementation.

Large doses of intravenous terbutaline have been reported to aggravate pre-existing diabetes mellitus and ketoacidosis.

Drug Interactions
The concomitant use of terbutaline sulfate injection with other sympathomimetic agents is not recommended, since the combined effect on the cardiovascular system may be deleterious to the patient.

Monoamine Oxidase Inhibitors or Tricyclic Antidepressants:Terbutaline should be administered with extreme caution to patients being treated with monoamine oxidase inhibitors or tricyclic antidepressants, or within 2 weeks of discontinuation of such agents, since the action of terbutaline on the vascular system may be potentiated.

Beta-Blockers: Beta-adrenergic receptor blocking agents not only block the pulmonary effect of beta-agonists, such as terbutaline sulfate injection, but may produce severe bronchospasm in asthmatic patients. Therefore, patients with asthma should not normally be treated with beta‑blockers. However, under certain circumstances, e.g., as prophylaxis after myocardial infarction, there may be no acceptable alternatives to the use of beta-adrenergic blocking agents in patients with asthma. In this setting, cardioselective betablockers could be considered, although they should be administered with caution.

Diuretics: The ECG changes and/or hypokalemia that may result from the administration of nonpotassium-sparing diuretics (such as loop or thiazide diuretics) can be acutely worsened by beta-agonists, especially when the recommended dose of the beta-agonist is exceeded. Although the clinical significance of these effects is not known, caution is advised in the coadministration of beta-agonists with nonpotassium-sparing diuretics.

Carcinogenesis, Mutagenesis, Impairment of Fertility
In a 2-year study in Sprague-Dawley rats, terbutaline sulfate caused a significant and dose‑related increase in the incidence of benign leiomyomas of the mesovarium at dietary doses of 50 mg/kg and above (approximately 810 times the maximum recommended daily subcutaneous (sc) dose for adults on a mg/m2 basis). In a 21-month study in CD-1 mice, terbutaline sulfate showed no evidence of tumorigenicity at dietary doses up to 200 mg/kg (approximately 1,600 times the maximum recommended daily sc dose for adults on a mg/m^2 basis). The mutagenicity potential of terbutaline sulfate has not been determined.

Reproduction studies in rats using terbutaline sulfate demonstrated no impairment of fertility at oral doses up to 50 mg/kg (approximately 810 times the maximum recommended daily sc dose for adults on a mg/m2 basis).

Pregnancy -Teratogenic Effects
There are no adequate and well-controlled studies of terbutaline sulfate in pregnant women. Published animal studies show that rat offspring exhibit alterations in behavior and brain development, including decreased cellular proliferation and differentiation when dams were treated subcutaneously with terbutaline during the late stage of pregnancy and lactation period. Terbutaline exposures in rat dams were approximately 24 to 48 times the common human dose in adults of 2-4 mg/day, on a mg/m2 basis.

Terbutaline sulfate has not been approved and should not be used for prolonged tocolysis (beyond 48-72 hours). In particular, terbutaline sulfate should not be used for maintenance tocolysis in the outpatient or home setting. Serious adverse reactions, including death, have been reported after administration of terbutaline sulfate to pregnant women. In the mother, these adverse reactions include increased heart rate, transient hyperglycemia, hypokalemia, cardiac arrhythmias, pulmonary edema and myocardial ischemia. Increased fetal heart rate and neonatal hypoglycemia may occur as a result of maternal administration (see BOXED WARNING: Prolonged Tocolysis and CONTRAINDICATIONS: Prolonged Tocolysis).

In animal embryofetal developmental studies, no teratogenic effects were observed in offspring when pregnant rats and rabbits received terbutaline sulfate at oral doses up to 50 mg/kg/day, approximately 810 and 1,600 times, respectively, the maximum recommended daily subcutaneous dose for adults, on a mg/m^2 basis.

Terbutaline sulfate should be used during pregnancy only if the potential benefits justify the potential risk to the fetus.

Use In Labor and Delivery
Because of the potential for beta-agonist interference with uterine contractility, use of terbutaline sulfate injection for relief of bronchospasm during labor should be restricted to those patients in whom the benefits clearly outweigh the risk.

Terbutaline crosses the placenta. After single dose IV administration of terbutaline to 22 women in late pregnancy who were delivered by elective Cesarean section due to clinical reasons, umbilical blood levels of terbutaline were found to range from 11% to 48% of the maternal blood levels.

Nursing Mothers
It is not known whether this drug is excreted in human milk. Therefore, terbutaline sulfate injection should be used during nursing only if the potential benefit justifies the possible risk to the newborn.

Pediatric Use
Terbutaline sulfate injection is not recommended for patients under the age of 12 years because of insufficient clinical data to establish safety and effectiveness.

Geriatric Use
Clinical studies of terbutaline sulfate injection did not include sufficient numbers of subjects aged 65 and over to determine whether they respond differently from younger subjects. Other reported clinical experience has not identified differences in responses between the elderly and younger patients. In general, dose selection for an elderly patient should be cautious, usually starting at the low end of the dosing range, reflecting the greater frequency of decreased hepatic, renal, or cardiac function, and of concomitant disease or other drug therapy.

Adverse Reactions

Adverse reactions observed with terbutaline sulfate injection are similar to those commonly seen with other sympathomimetic agents. All these reactions are transient in nature and usually do not require treatment.

The following table compares adverse reactions seen in patients treated with terbutaline sulfate injection (0.25 mg and 0.5 mg), with those seen in patients treated with epinephrine injection (0.25 mg and 0.5 mg), during eight double-blind crossover studies involving a total of 214 patients.

Note: Some patients received more than one dosage strength of terbutaline sulfate and epinephrine. In addition, there were reports of anxiety, muscle cramps, and dry mouth (< 0.5%). There have been rare reports of elevations in liver enzymes and of hypersensitivity vasculitis with terbutaline administration.

To report SUSPECTED ADVERSE REACTIONS, contact Hikma Pharmaceuticals USA Inc. at 1-877-845-0689, or the FDA at 1-800-FDA-1088 or www.fda.gov/medwatch.

Overdosage

The median sc lethal dose of terbutaline sulfate in mature rats was approximately 165 mg/kg (approximately 2,700 times the maximum recommended daily sc dose for adults on a mg/m^2 basis). The median sc lethal dose of terbutaline sulfate in young rats was approximately 2,000 mg/kg (approximately 32,000 times the maximum recommended daily sc dose for adults on a mg/m^2 basis).

The expected symptoms with overdosage are those of excessive beta-adrenergic stimulation and/or occurrence or exaggeration of any of the symptoms listed under ADVERSE REACTIONS, e.g., seizures, angina, hypertension or hypotension, tachycardia with rates up to 200 beats per minute, arrhythmias, nervousness, headache, tremor, dry mouth, palpitation, nausea, dizziness, fatigue, malaise, and insomnia. Hypokalemia may also occur. There is no specific antidote. Treatment consists of discontinuation of terbutaline sulfate injection together with appropriate symptomatic therapy. The judicious use of a cardioselective beta-receptor blocker may be considered, bearing in mind that such medication can produce bronchospasm. There is insufficient evidence to determine if dialysis is beneficial for overdosage of terbutaline sulfate injection.

Dosage and Administration

Vials should be used only for subcutaneous administration and not intravenous infusion.

Sterility and accurate dosing cannot be assured if the vials are not used in accordance with DOSAGE AND ADMINISTRATION.

Discard unused portion after single patient use.

The usual subcutaneous dose of terbutaline sulfate injection is 0.25 mg injected into the lateral deltoid area. If significant clinical improvement does not occur within 15 to 30 minutes, a second dose of 0.25 mg may be administered. If the patient then fails to respond within another 15 to 30 minutes, other therapeutic measures should be considered. The total dose within 4 hours should not exceed 0.5 mg.

Note: Parenteral drug products should be inspected visually for particulate matter and discoloration prior to administration, whenever solution and container permit.

How Supplied

Terbutaline Sulfate Injection, USP, 1 mg/mL, is supplied at a volume of 1 mL contained in a 2 mL amber glass vial. Each vial contains 1 mg of terbutaline sulfate per 1 mL of solution; 0.25 mL of solution will provide the usual clinical dose of 0.25 mg.

NDC 0143-9746-10 Carton of 10 vials.

Store at 20° to 25°C (68° to 77°F) [See USP Controlled Room Temperature].

Protect from light by storing vials in original carton until dispensed.

Do not use if solution is discolored.

Discard unused portion after single patient use.

Product repackaged by: Henry Schein, Inc., Bastian, VA 24314
From Original Manufacturer/Distributor's NDC and Unit of Sale | To Henry Schein Repackaged Product NDC and Unit of Sale | Total Strength/Total Volume (Concentration) per unit
NDC 0143-9746-10 Carton of 10 vials | NDC 0404-9778-01 1 1 mL Vial in a bag (Vial bears NDC 0143-9746-01) | 1 mg/mL

Manufactured by:
HIKMA FARMACÊUTICA (PORTUGAL), S.A..
Estrada do Rio da Mó, nº 8, 8A e 8B - Fervença,
2705 906 Terrugem SNT,
PORTUGAL

Distributed by:
Hikma Pharmaceuticals USA Inc.
Berkeley Heights, NJ 07922

Revised: February 2021

PIN217-WES/4